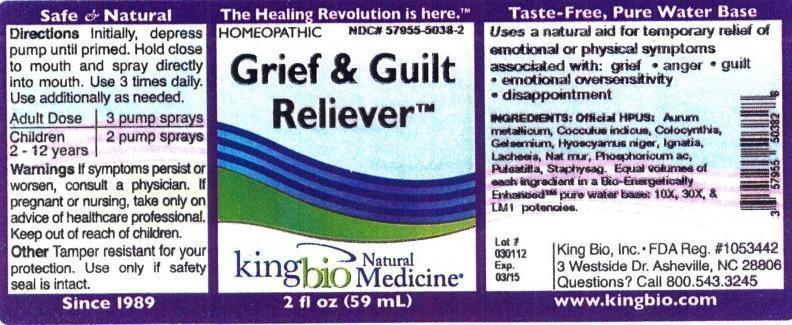 DRUG LABEL: Grief and Guilt Reliever
NDC: 57955-5038 | Form: LIQUID
Manufacturer: King Bio Inc.
Category: homeopathic | Type: HUMAN OTC DRUG LABEL
Date: 20120817

ACTIVE INGREDIENTS: GOLD 10 [hp_X]/59 mL; ANAMIRTA COCCULUS SEED 10 [hp_X]/59 mL; CITRULLUS COLOCYNTHIS FRUIT PULP 10 [hp_X]/59 mL; GELSEMIUM SEMPERVIRENS ROOT 10 [hp_X]/59 mL; HYOSCYAMUS NIGER 10 [hp_X]/59 mL; STRYCHNOS IGNATII SEED 10 [hp_X]/59 mL; LACHESIS MUTA VENOM 10 [hp_X]/59 mL; SODIUM CHLORIDE 10 [hp_X]/59 mL; PHOSPHORIC ACID 10 [hp_X]/59 mL; PULSATILLA VULGARIS 10 [hp_X]/59 mL; DELPHINIUM STAPHISAGRIA SEED 10 [hp_X]/59 mL
INACTIVE INGREDIENTS: WATER

Grief and Guilt Reliever

Active Ingredients

Official HPUS: Aurum metallicum, Cocculus indicus, Colocynthis, Gelsemium sempervirens, Hyoscyamus niger, Ignatia amara, Lachesis mutus, Natrum muriaticum, Phosphoricum acidum, Pulsatilla, Staphysagria

Inactive Ingredient

Equal volumes of each ingredient in a Bio-Energetically Enhanced pure water base: 10X, 30X, and LM1 potencies.

Purpose

Uses a natural aid for temporary relief of emotional or physical symptoms associated with:

- grief
- anger
- guilt
- emotional oversensitivity
- disappointment

Dosage and Administration

Directions: Initially, depress pump until primed. Hold close to mouth and spray directly into mouth. Use 3 times daily. Use additionally as needed.

Adult Dose 3 pump sprays

Children 2 - 12 years 2 pump sprays

Warnings

If symptoms persist or worsen, consult a physician. If pregnant or nursing, take only on advice of healthcare professional. Keep out of reach of children.

Other: Tamper resistant for your protection. Use only if safety seal is intact.

Keep out of reach of children.

Indications and Usage

Uses a natural aid for temporary relief of emotional or physical symptoms associated with: grief, anger, guilt, emotional oversensitivity, disappointment.

PACKAGE LABEL

King Bio Inc.

3 Westside Drive

Asheville, NC 28806

Questions? Call 800.543.3245

www.kingbio.com